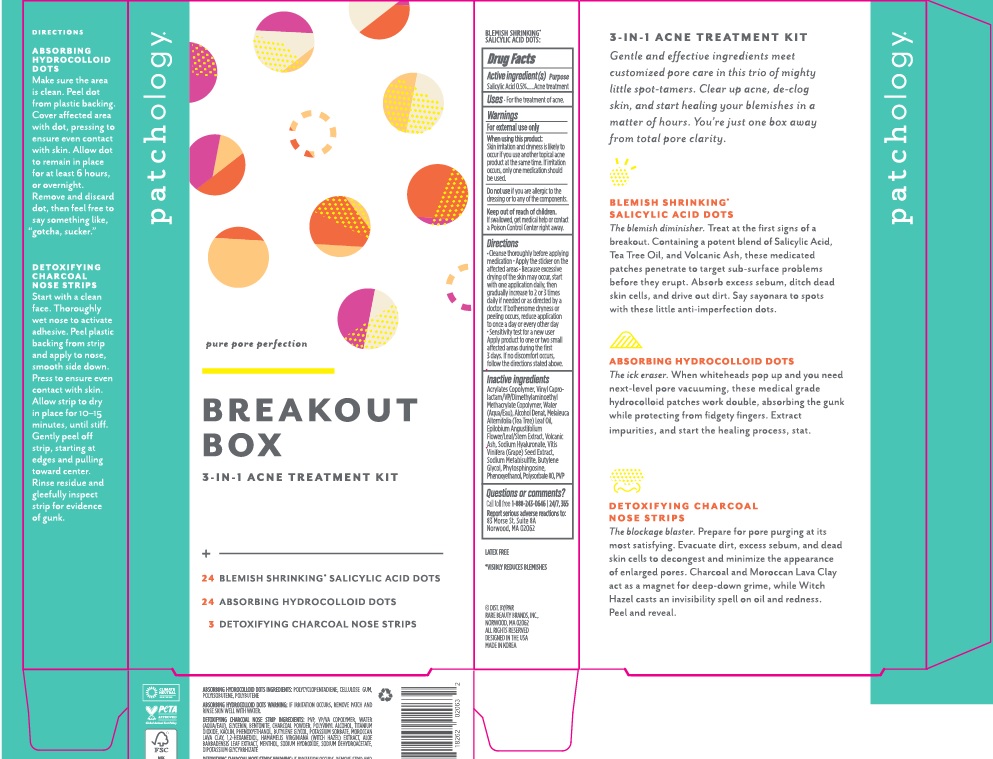 DRUG LABEL: PATCHOLOGY BREAKOUT BOX 3-IN-1 ACNE TREATMENT
NDC: 72204-002 | Form: KIT | Route: TOPICAL
Manufacturer: Iontera, Inc
Category: otc | Type: HUMAN OTC DRUG LABEL
Date: 20241203

ACTIVE INGREDIENTS: SALICYLIC ACID 5 mg/1 g
INACTIVE INGREDIENTS: PHYTOSPHINGOSINE; PHENOXYETHANOL; POLYSORBATE 80; POVIDONE; BUTYL ACRYLATE/METHYL METHACRYLATE/METHACRYLIC ACID COPOLYMER (18000 MW); ALCOHOL; EPILOBIUM ANGUSTIFOLIUM FLOWERING TOP; HYALURONATE SODIUM; VITIS VINIFERA SEED; BUTYLENE GLYCOL; WATER; TEA TREE OIL; SODIUM METABISULFITE

PATCHOLOGY BREAKOUT BOX 3-IN-1 ACNE TREATMENT KIT

Active ingredient(s)

Salicylic Acid 0.5%

Purpose

Acne Treatment

Use

For the treatment of acne

Warnings

For external use only

When using this product skin irritation and dryness is likely to occur if you use another topical acne product at the same time. If irritation occurs, only one medication should be used.

Do not use if you are allergic to the dressing or to any of the components.

Keep out of reach of children. If swallowed, get medical help or contact a Poison Control Center right away.

Directions

- Cleanse thoroughly before applying medication.
- Apply the sticker on the affected areas. Because excessive drying of the skin may occur, start with one application daily, then gradually increase to 2 or 3 times daily if needed or as directed by a doctor. If bothersome dyrness or peeling occurs, reduce application to once a day or every other day.
- Sensitivity test for a new user: Apply product to one or two small affected areas during the first 3 days. If no discomfort occurs, follow the directions stated above.

Inactive ingredients

Acrylates Copolymer, Vinyl Caprolactam/VP/Dimethylaminoethyl Methacrylate Copolymer, Water (Aqua/Eau), Alcohol Denat., Melaleuca Alternifolia (Tea Tree) Leaf Oil, Epilobium Angustifolium Flower/Leaf/Stem Extract, Volcanic Ash, Sodium Hyaluronate, Vitis Vinifera (Grape) Seed Extract, Sodium Metabisulfite, Butylene Glycol, Phytosphingosine, Phenoxyethanol, Polysorbate 80, PVP.

Questions or comments?

Call toll free 1-888-243-0646 24/7, 365

Report serious adverse reactions to: 83 Morse St. Suite 8A Norwood, MA 02062

Company Information

DIST. BY RARE BEAUTY BRANDS, INC.

NORWOOD, MA 02062

DESIGNED IN THE USA

MADE IN KOREA